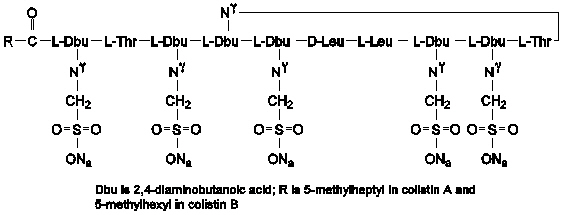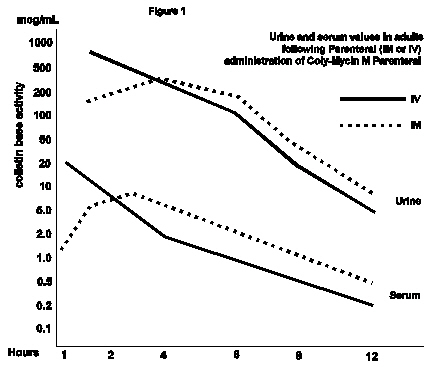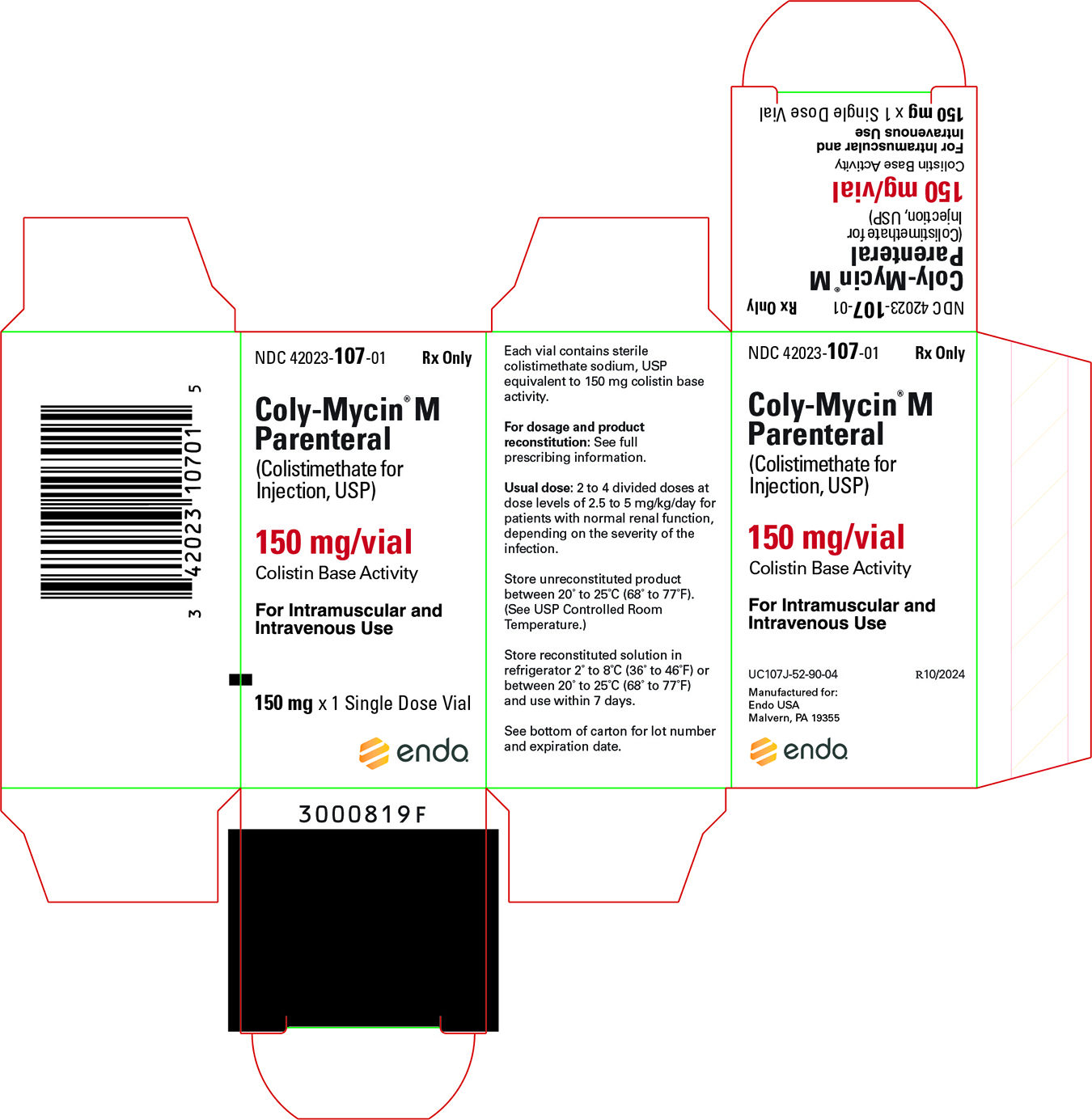 DRUG LABEL: Coly-Mycin
NDC: 42023-107 | Form: INJECTION
Manufacturer: Endo USA, Inc.
Category: prescription | Type: HUMAN PRESCRIPTION DRUG LABEL
Date: 20250423

ACTIVE INGREDIENTS: COLISTIMETHATE SODIUM 150 mg/2 mL

Coly-Mycin® M Parenteral (Colistimethate for Injection, USP)

To reduce the development of drug-resistant bacteria and maintain the effectiveness of Coly-Mycin M and other antibacterial drugs, Coly-Mycin M should be used only to treat or prevent infections that are proven or strongly suspected to be caused by bacteria.

FOR INTRAMUSCULAR AND INTRAVENOUS USE

DESCRIPTION

Coly-Mycin® M Parenteral (Colistimethate for Injection, USP) is a sterile parenteral antibiotic product which, when reconstituted (see Reconstitution), is suitable for intramuscular or intravenous administration.

Each vial contains colistimethate sodium or pentasodium colistinmethanesulfonate (150 mg colistin base activity).

Colistimethate sodium is a polypeptide antibiotic with an approximate molecular weight of 1750. The empirical formula is C58H105N16Na5O28S5 and the structural formula is represented below:

CLINICAL PHARMACOLOGY

Typical serum and urine levels following a single 150 mg dose of Coly-Mycin M Parenteral IM or IV in normal adult subjects are shown in Figure 1.

Higher serum levels were obtained at 10 minutes following IV administration. Serum concentration declined with a half-life of 2–3 hours following either intravenous or intramuscular administration in adults and in the pediatric population, including premature infants.

Average urine levels ranged from about 270 mcg/mL at 2 hours to about 15 mcg/mL at 8 hours after intravenous administration and from 200 to about 25 mcg/mL during a similar period following intramuscular administration.

Microbiology:

Colistimethate sodium is a surface active agent which penetrates into and disrupts the bacterial cell membrane. It has been shown to have bactericidal activity against most strains of the following microorganisms, both in vitro and in clinical infections as described in the INDICATIONS AND USAGE section:

Aerobic gram-negative microorganisms: Enterobacter aerogenes, Escherichia coli, Klebsiella pneumoniae and Pseudomonas aeruginosa.

Susceptibility Testing: For specific information regarding susceptibility test interpretive criteria and associated test methods and quality control standards recognized by FDA for this drug, please see: https://www.fda.gov/STIC.

INDICATIONS AND USAGE

Coly-Mycin M Parenteral is indicated for the treatment of acute or chronic infections due to sensitive strains of certain gram-negative bacilli. It is particularly indicated when the infection is caused by sensitive strains of Pseudomonas aeruginosa. This antibiotic is not indicated for infections due to Proteus or Neisseria. Coly-Mycin M Parenteral has proven clinically effective in treatment of infections due to the following gram-negative organisms: Enterobacter aerogenes, Escherichia coli, Klebsiella pneumoniae and Pseudomonas aeruginosa.

Coly-Mycin M Parenteral may be used to initiate therapy in serious infections that are suspected to be due to gram-negative organisms and in the treatment of infections due to susceptible gram-negative pathogenic bacilli.

To reduce the development of drug-resistant bacteria and maintain the effectiveness of Coly-Mycin M and other antibacterial drugs, Coly-Mycin M should be used only to treat or prevent infections that are proven or strongly suspected to be caused by susceptible bacteria. When culture and susceptibility information are available, they should be considered in selecting or modifying antibacterial therapy. In the absence of such data, local epidemiology and susceptibility patterns may contribute to the empiric selection of therapy.

CONTRAINDICATIONS

The use of Coly-Mycin M Parenteral is contraindicated for patients with a history of sensitivity to the drug or any of its components.

WARNINGS

Maximum daily dose calculated from colistin base activity should not exceed 5 mg/kg/day with normal renal function.

Transient neurological disturbances may occur. These include circumoral paresthesia or numbness, tingling or formication of the extremities, generalized pruritus, vertigo, dizziness, and slurring of speech. For these reasons, patients should be warned not to drive vehicles or use hazardous machinery while on therapy. Reduction of dosage may alleviate symptoms. Therapy need not be discontinued, but such patients should be observed with particular care.

Nephrotoxicity can occur and is probably a dose-dependent effect of colistimethate sodium. These manifestations of nephrotoxicity are reversible following discontinuation of the antibiotic.

Electrolyte and Acid/Base Abnormalities

Postmarketing cases of renal tubulopathy (i.e., Pseudo-Bartter syndrome) have been identified with the use of intravenous colistimethate sodium (see ADVERSE REACTIONS). All cases reported hypokalemia and metabolic alkalosis. Other common findings included hypocalcemia, hypomagnesemia, increased potassium in the urine, normal serum creatinine, and normal blood pressure. Consider electrolyte monitoring during treatment. Normalization of electrolyte abnormalities may require drug discontinuation.

Overdosage can result in renal insufficiency, muscle weakness, and apnea (see OVERDOSAGE section). See PRECAUTIONS, Drug Interactions subsection for use concomitantly with other antibiotics and curariform drugs.

Respiratory arrest has been reported following intramuscular administration of colistimethate sodium. Impaired renal function increases the possibility of apnea and neuromuscular blockade following administration of colistimethate sodium. Therefore, it is important to follow recommended dosing guidelines. See DOSAGE AND ADMINISTRATION section for use in renal impairment.

Clostridium difficile associated diarrhea (CDAD) has been reported with use of nearly all antibacterial agents, including Coly-Mycin M Parenteral, and may range in severity from mild diarrhea to fatal colitis. Treatment with antibacterial agents alters the normal flora of the colon leading to overgrowth of C. difficile.

C. difficile produces toxins A and B which contribute to the development of CDAD. Hypertoxin producing strains of C. difficile cause increased morbidity and mortality, as these infections can be refractory to antimicrobial therapy and may require colectomy. CDAD must be considered in all patients who present with diarrhea following antibiotic use. Careful medical history is necessary since CDAD has been reported to occur over two months after the administration of antibacterial agents.

If CDAD is suspected or confirmed, ongoing antibiotic use not directed against C. difficile may need to be discontinued. Appropriate fluid and electrolyte management, protein supplementation, antibiotic treatment of C. difficile, and surgical evaluation should be instituted as clinically indicated.

PRECAUTIONS

General

Since Coly-Mycin M Parenteral is eliminated mainly by renal excretion, it should be used with caution when the possibility of impaired renal function exists. The decline in renal function with advanced age should be considered.

When actual renal impairment is present, Coly-Mycin M Parenteral may be used, but the greatest caution should be exercised and the dosage should be reduced in proportion to the extent of the impairment. Administration of amounts of Coly-Mycin M Parenteral in excess of renal excretory capacity will lead to high serum levels and can result in further impairment of renal function, initiating a cycle which, if not recognized, can lead to acute renal insufficiency, renal shutdown, and further concentration of the antibiotic to toxic levels in the body. At this point, interference of nerve transmission at neuromuscular junctions may occur and result in muscle weakness and apnea (see OVERDOSAGE section).

Signs indicating the development of impaired renal function include: diminishing urine output, rising BUN and serum creatinine and decreased creatinine clearance. Therapy with Coly-Mycin M Parenteral should be discontinued immediately if signs of impaired renal function occur. However, if it is necessary to reinstate the drug, dosing should be adjusted accordingly after drug plasma levels have fallen (see DOSAGE AND ADMINISTRATION section).

Prescribing Coly-Mycin M in the absence of a proven or strongly suspected bacterial infection or a prophylactic indication is unlikely to provide benefit to the patient and increases the risk of the development of drug-resistant bacteria.

Drug Interactions

Certain other antibiotics (aminoglycosides and polymyxin) have also been reported to interfere with the nerve transmission at the neuromuscular junction. Based on this reported activity, they should not be given concomitantly with Coly-Mycin M Parenteral except with the greatest caution.

Curariform muscle relaxants (e.g., tubocurarine) and other drugs, including ether, succinylcholine, gallamine, decamethonium and sodium citrate, potentiate the neuromuscular blocking effect and should be used with extreme caution in patients being treated with Coly-Mycin M Parenteral.

Sodium cephalothin may enhance the nephrotoxicity of Coly-Mycin M Parenteral. The concomitant use of sodium cephalothin and Coly-Mycin M Parenteral should be avoided.

Carcinogenesis, Mutagenesis, Impairment of Fertility

Long-term animal carcinogenicity studies and genetic toxicology studies have not been performed with colistimethate sodium. There were no adverse effects on fertility or reproduction in rats at doses of 9.3 mg/kg/day (0.30 times the maximum daily human dose when based on mg/m^2).

Pregnancy - Teratogenic Effects

Colistimethate sodium given intramuscularly during organogenesis to rabbits at 4.15 and 9.3 mg/kg resulted in talipes varus in 2.6% and 2.9% of fetuses, respectively. These doses are 0.25 and 0.55 times the maximum daily human dose based on mg/m^2. In addition, increased resorption occurred at 9.3 mg/kg. Colistimethate sodium was not teratogenic in rats at 4.15 or 9.3 mg/kg. These doses are 0.13 and 0.30 times the maximum daily human dose based on mg/m^2. There are no adequate and well-controlled studies in pregnant women. Since colistimethate sodium is transferred across the placental barrier in humans, it should be used during pregnancy only if the potential benefit justifies the potential risk to the fetus.

Nursing Mothers

It is not known whether colistimethate sodium is excreted in human breast milk. However, colistin sulphate is excreted in human breast milk. Therefore, caution should be exercised when colistimethate sodium is administered to nursing women.

Geriatric Use

Clinical studies of colistimethate sodium did not include sufficient numbers of subjects aged 65 and over to determine whether they respond differently from younger subjects. Other reported clinical experience has not identified differences in responses between the elderly and younger patients. In general, dose selection for an elderly patient should be cautious, usually starting at the low end of the dosing range, reflecting the greater frequency of decreased hepatic, renal, or cardiac function, and of concomitant disease or other drug therapy. This drug is known to be substantially excreted by the kidney, and the risk of toxic reactions to this drug may be greater in patients with impaired renal function. Because elderly patients are more likely to have decreased renal function, care should be taken in dose selection, and it may be useful to monitor renal function.

Pediatric Use

In clinical studies, colistimethate sodium was administered to the pediatric population (neonates, infants, children and adolescents). Although adverse reactions appear to be similar in the adult and pediatric populations, subjective symptoms of toxicity may not be reported by pediatric patients. Close clinical monitoring of pediatric patients is recommended.

Information for Patients

Patients should be counseled that antibacterial drugs including Coly-Mycin M should only be used to treat bacterial infections. They do not treat viral infections (e.g., the common cold). When Coly-Mycin M is prescribed to treat a bacterial infection, patients should be told that although it is common to feel better early in the course of therapy, the medication should be taken exactly as directed. Skipping doses or not completing the full course of therapy may (1) decrease the effectiveness of the immediate treatment and (2) increase the likelihood that bacteria will develop resistance and will not be treatable by Coly-Mycin M or other antibacterial drugs in the future.

Diarrhea is a common problem caused by antibiotics which usually ends when the antibiotic is discontinued. Sometimes after starting treatment with antibiotics, patients can develop watery and bloody stools (with or without stomach cramps and fever) even as late as two or more months after having taken the last dose of the antibiotic. If this occurs, patients should contact their physician as soon as possible.

ADVERSE REACTIONS

The following adverse reactions have been reported:

Gastrointestinal: gastrointestinal upset

Nervous System: tingling of extremities and tongue, slurred speech, dizziness, vertigo, paresthesia, and seizures

Integumentary: generalized itching, urticaria and rash

Body as a Whole: fever and anaphylaxis

Laboratory Deviations: increased blood urea nitrogen (BUN), elevated creatinine and decreased creatinine clearance

Respiratory System: respiratory distress and apnea

Renal System: electrolyte and acid/base abnormalities (i.e., Pseudo-Bartter syndrome), nephrotoxicity and decreased urine output

For medical advice about adverse reactions contact your medical professional. To report SUSPECTED ADVERSE REACTIONS, contact Endo at 1-800-828-9393 or FDA at 1-800-FDA-1088 or www.fda.gov/medwatch.

OVERDOSAGE

Overdosage with colistimethate sodium can cause neuromuscular blockade characterized by paresthesia, lethargy, confusion, dizziness, ataxia, nystagmus, disorders of speech and apnea. Respiratory muscle paralysis may lead to apnea, respiratory arrest and death. Overdosage with the drug can also cause acute renal failure, manifested as decreased urine output and increases in serum concentrations of BUN and creatinine.

As in any case of overdose, colistimethate sodium therapy should be discontinued and general supportive measures should be utilized.

It is unknown whether colistimethate sodium can be removed by hemodialysis or peritoneal dialysis in overdose cases.

DOSAGE AND ADMINISTRATION

Important: Coly-Mycin M Parenteral is supplied in vials containing colistimethate sodium equivalent to 150 mg colistin base activity per vial.

Reconstitution for Intravenous or Intramuscular Administration:

The 150 mg vial should be reconstituted with 2 mL Sterile Water for Injection, USP. The reconstituted solution provides colistimethate sodium at a concentration equivalent to 75 mg/mL colistin base activity.

During reconstitution swirl gently to avoid frothing.

Parenteral drug products should be inspected visually for particulate matter and discoloration prior to administration, whenever solution and container permit. If these conditions are observed, the product should not be used.

Dosage

Adults and Pediatric Patients—Intravenous or Intramuscular Administration:

The dose of Coly-Mycin M Parenteral should be 2.5 to 5 mg/kg per day of colistin base in 2 to 4 divided doses for patients with normal renal function, depending on the severity of the infection.

In obese individuals, dosage should be based on ideal body weight.

The daily dose and frequency should be reduced for the patients with renal impairment. Suggested modifications of dosage schedule for patients with renal impairment are presented in Table 1.

TABLE 1. Suggested Modification of Dosage Schedules of Coly-Mycin M Parenteral for Adults with Impaired Renal Function
 | Degree of Renal Impairment
 | Normal | Mild | Moderate | Severe
Creatinine Clearance (mL/min) | ≥80 | 50-79 | 30-49 | 10-29
Dosage Schedule | 2.5 – 5 mg/kg, divided into 2 to 4 doses per day | 2.5 – 3.8 mg/kg, divided into 2 doses per day | 2.5 mg/kg, once daily or divided into 2 doses per day | 1.5 mg/kg every 36 hours
Note: The suggested total daily dose is calculated from colistin base activity.

INTRAVENOUS ADMINISTRATION

1. Direct Intermittent Administration—Slowly inject one-half of the total daily dose over a period of 3 to 5 minutes every 12 hours.

2. Continuous Infusion—Slowly inject one-half of the total daily dose over 3 to 5 minutes. Add the remaining half of the total daily dose of Coly-Mycin M Parenteral to one of the following:
0.9% NaCl
5% dextrose in 0.9% NaCl
5% dextrose in water
5% dextrose in 0.45% NaCl
5% dextrose in 0.225% NaCl
lactated Ringer's solution
10% invert sugar solution

There are not sufficient data to recommend usage of Coly-Mycin M Parenteral with other drugs or other than the above listed infusion solutions.

Administer the second half of the total daily dose by slow intravenous infusion, starting 1 to 2 hours after the initial dose, over the next 22 to 23 hours. In the presence of impaired renal function, reduce the infusion rate depending on the degree of renal impairment.

The choice of intravenous solution and the volume to be employed are dictated by the requirements of fluid and electrolyte management.

Any final intravenous infusion solution containing colistimethate sodium should be freshly prepared and used for no longer than 24 hours.

INTRAMUSCULAR ADMINISTRATION

1. For Intramuscular Injection, administer by deep intramuscular injection into a large muscle mass (such as the gluteal muscles or lateral part of the thigh).

Store reconstituted solution for intramuscular injection in a refrigerator 2° to 8°C (36° to 46°F) or between 20° to 25°C (68° to 77°F) and use within 7 days.

HOW SUPPLIED

Coly-Mycin M Parenteral is supplied in vials containing colistimethate sodium (equivalent to 150 mg colistin base activity per vial) as a white to slightly yellow lyophilized cake.

NDC 42023-107-01: one individual vial.

STORAGE AND HANDLING

Store unreconstituted product between 20° to 25°C (68° to 77°F). (See USP Controlled Room Temperature.)

Store reconstituted solution in refrigerator 2° to 8°C (36° to 46°F) or between 20° to 25°C (68° to 77°F) and use within 7 days.

Rx only.

Manufactured for:
Endo USA
Malvern, PA 19355

© 2025 Endo, Inc. or one of its affiliates.

R04/2025

PRINCIPAL DISPLAY PANEL - 150 mg Vial Carton

NDC 42023-107-01

Coly-Mycin® M
Parenteral
(Colistimethate for
Injection, USP

150 mg
Colistin base
activity

For Intramuscular and
Intravnous Use

Rx Only

1 Vial